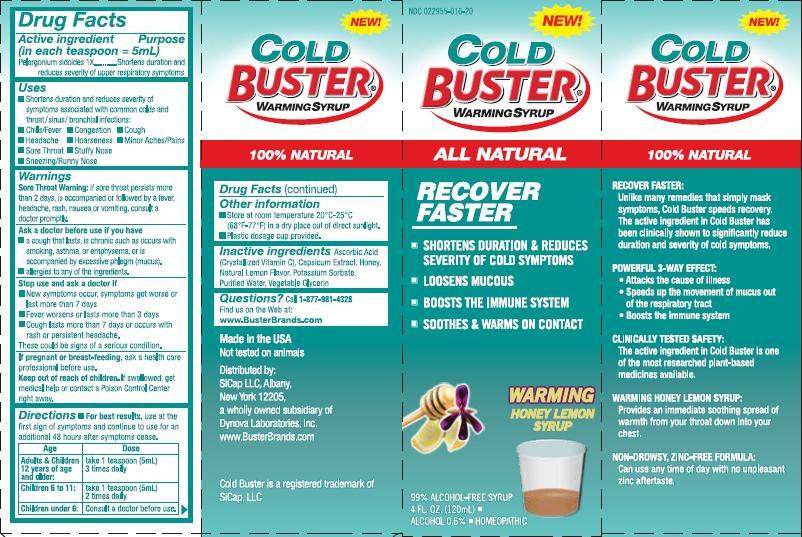 DRUG LABEL: Cold Buster
NDC: 22955-016 | Form: SYRUP
Manufacturer: SiCap Industries LLC
Category: homeopathic | Type: HUMAN OTC DRUG LABEL
Date: 20100413

ACTIVE INGREDIENTS: PELARGONIUM SIDOIDES ROOT 24 [hp_X]/120 mL

INDICATIONS AND USAGE

- Shortens duration and reduces severity of symptoms associated with common colds and throat/sinus/bronchial infections:
- Chills/Fevers
- Headache
- Sore Throat
- Sneezing/Runny Nose
- Congestion
- Hoarseness
- Stuffy Nose
- Cough
- Minor Aches/Pains

Warnings

Sore Throat Warning: if sore throat persists more than 2 days, is accompanied or followed by a fever, headache, rash, nausea or vomitting, consult a doctor promptly.

Ask a doctor before use if you have:

- a cough that lasts, is chronic such as occurs with smoking, asthma, or emphysema, or is accompanied by excessive phlegm (mucus).
- allergies to any of the ingredients

Stop use and ask a doctor if:

- New symptoms occur, symptoms get worse or last more than 7 days
- Fever worsens or lasts more than 3 days
- Cough lasts more than 7 days or occurs with rash or persistent headache

These could be signs of a serious condition.

PREGNANCY OR BREAST FEEDING

If pregnant or breast-feeding, ask a health care professional before use.

Keep out of reach of children. If swallowed, get medical help or contact a Poison Control Center right away.

Directions:

For best results, use at the first sign of symptoms and continue to use for an additional 48 hours after symptoms cease.
Age Dose
Adults and Children take 1 teaspoon (5ml)
12 years of age 3 times daily
and older:
Children 6 to 11: take 1 teaspoon (5ml)
2 times daily
Children under 6: Consult a doctor before use.

STORAGE AND HANDLING

- Store at room temperature 20-25 degrees C (68 to 77 degrees F) in a dry place out of direct sunlight
- Plastic dosage cup provided

INACTIVE INGREDIENT

Ascorbic Acid (Crystallized Vitamin C), Capsicum Extract, Honey, Natural Lemon Flavor, Potassium Sorbate, Purified Water, Vegetable Glycerin

Questions? Call 1-877-981-4328

Find us on the Web at:

www.BusterBrands.com

PACKAGE LABEL

Recover Faster

- Shortens duration and reduces severity of cold symptoms
- Loosens mucous
- Boosts the immune system
- Soothes and warms on contact

Recover Faster:
Unlike many remedies that simply mask symptoms, Cold Buster speeds recovery. The active ingredient in Cold Buster has been clinically shown to significantly reduce duration and severity of cold symptoms.
Powerful 3-way Effect:

- Attacks the cause of illness
- Speeds up the movement of mucus out of the respiratory tract
- Boosts the immune system

Clinical Tested Safety:
The active ingredient in Cold Buster is one of the most researched plant-based medicines available.
Warming Honey Lemon Syrup:
Provides an immediate soothing spread of warmth from your throat down into your chest.
Non-Drowsy, Zinc-Free Formula:
Can use any time of day with no unpleasant zinc aftertaste.
Made in the USA
Not tested on animals
Distributed by:
SiCap LLC, Albany,
New York 12205,
a wholly owned subsidiary of Dynova Laboratories, Inc.
www.BusterBrands.com

PURPOSE

Shortens duration and reduces severity of upper respiratory symptoms.